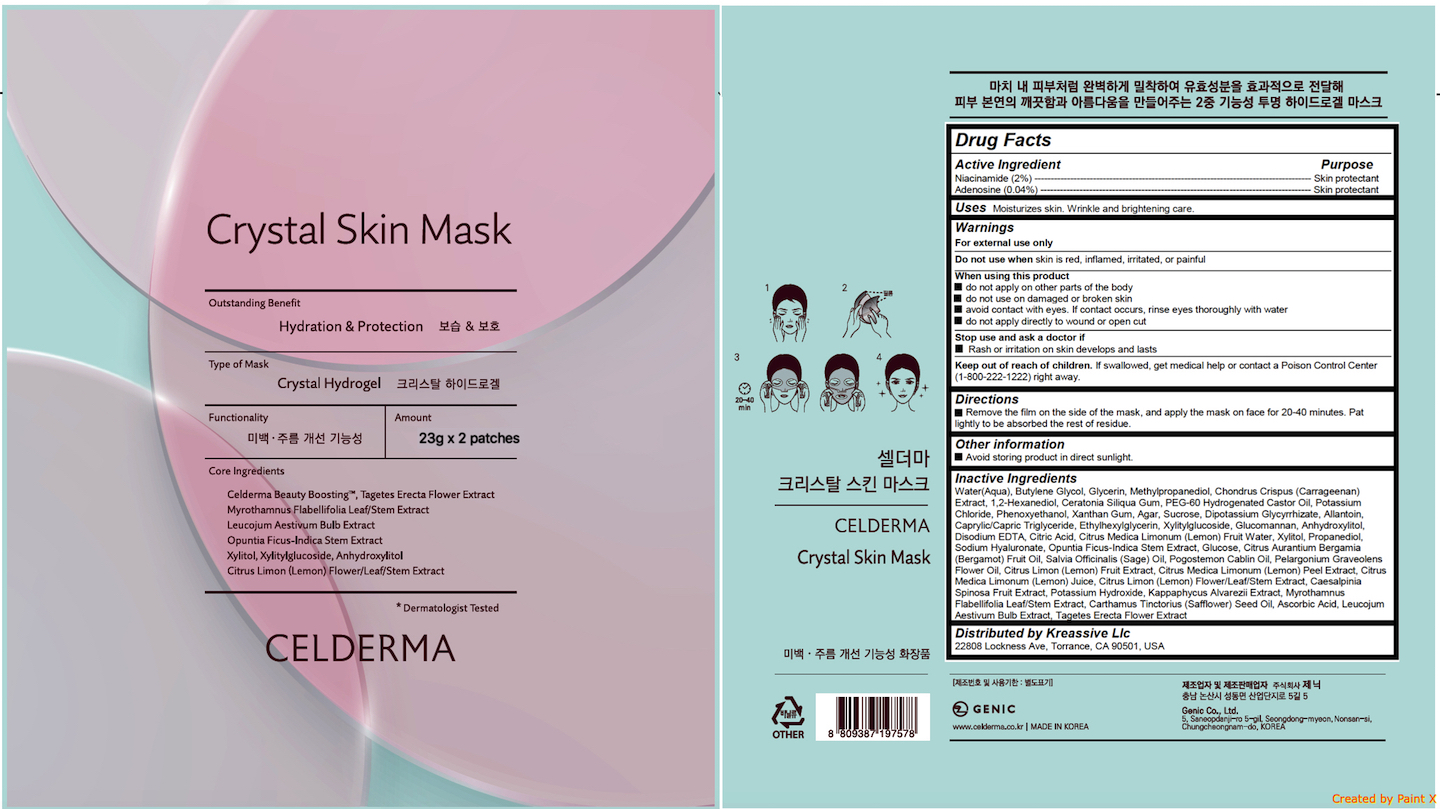 DRUG LABEL: CELDERMA Crystal Skin Mask
NDC: 72044-101 | Form: PATCH
Manufacturer: GENIC CO.,LTD
Category: otc | Type: HUMAN OTC DRUG LABEL
Date: 20180220

ACTIVE INGREDIENTS: NIACINAMIDE 0.46 g/23 g; ADENOSINE 0.0092 g/23 g
INACTIVE INGREDIENTS: METHYLPROPANEDIOL; 1,2-HEXANEDIOL; CHONDRUS CRISPUS CARRAGEENAN; PHENOXYETHANOL; WATER; BUTYLENE GLYCOL; GLYCERIN; PEG-60 HYDROGENATED CASTOR OIL; POTASSIUM CHLORIDE; XANTHAN GUM; LOCUST BEAN GUM

CELDERMA Crystal Skin Mask

Active ingredients

Niacinamide (2%)

Adenosine (0.04%)

Purpose

Skin protectant

Uses

Moisturizes skin. Wrinkle and brightening care.

Warnings

For external use only

Do not use when skin is red, inflamed, irritated, or painful

When using this product

do not apply on other parts of the body

do not use on damaged or broken skin

avoid contact with eyes. If contact occurs, rinse eyes thoroughly with water

do not apply directly to wound or open cut

Stop use and ask a doctor if

Rash or irritation on skin develops and lasts

Keep out of reach of chlldren

If swallowed, get medical help or contact a Poison Control Center (1-800-222-1222) right away.

Directions

Remove the film on the side of the mask, and apply the mask on face for 20-40 minutes. Pat lightly to be absorbed the rest of residue.

Inactive ingredients

Water(Aqua), Butylene Glycol, Glycerin, Methylpropanediol, Chondrus Crispus (Carrageenan) Extract, 1,2-Hexanediol, Ceratonia Siliqua Gum, PEG-60 Hydrogenated Castor Oil, Potassium Chloride, Phenoxyethanol, Xanthan Gum, Agar, Sucrose, Dipotassium Glycyrrhizate, Allantoin, Caprylic/Capric Triglyceride, Ethylhexylglycerin, Xylitylglucoside, Glucomannan, Anhydroxylitol, Disodium EDTA, Citric Acid, Citrus Medica Limonum (Lemon) Fruit Water, Xylitol, Propanediol, Sodium Hyaluronate, Opuntia Ficus-Indica Stem Extract, Glucose, Citrus Aurantium Bergamia (Bergamot) Fruit Oil, Salvia Officinalis (Sage) Oil, Pogostemon Cablin Oil, Pelargonium Graveolens Flower Oil, Citrus Limon (Lemon) Fruit Extract, Citrus Medica Limonum (Lemon) Peel Extract, Citrus Medica Limonum (Lemon) Juice, Citrus Limon (Lemon) Flower/Leaf/Stem Extract, Caesalpinia Spinosa Fruit Extract, Potassium Hydroxide, Kappaphycus Alvarezii Extract, Myrothamnus Flabellifolia Leaf/Stem Extract, Carthamus Tinctorius (Safflower) Seed Oil, Ascorbic Acid, Leucojum Aestivum Bulb Extract, Tagetes Erecta Flower Extract